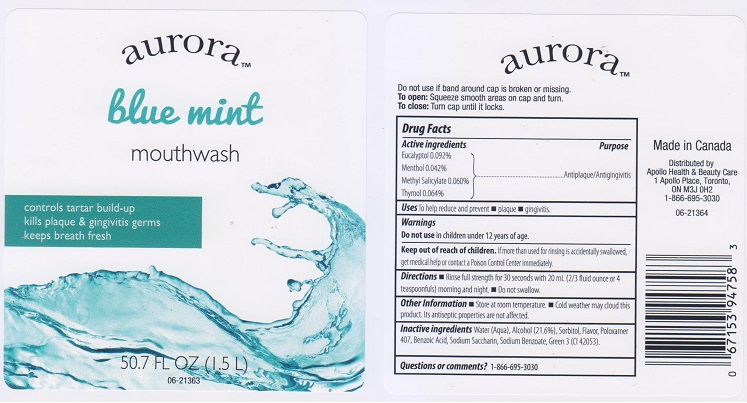 DRUG LABEL: Aurora Blue Mint
NDC: 63148-559 | Form: MOUTHWASH
Manufacturer: Apollo Health and Beauty Care
Category: otc | Type: HUMAN OTC DRUG LABEL
Date: 20160614

ACTIVE INGREDIENTS: EUCALYPTOL 0.92 mg/1 mL; MENTHOL 0.42 mg/1 mL; METHYL SALICYLATE 0.60 mg/1 mL; THYMOL 0.64 mg/1 mL
INACTIVE INGREDIENTS: WATER; ALCOHOL; SORBITOL; POLOXAMER 407; BENZOIC ACID; SACCHARIN SODIUM; SODIUM BENZOATE; FD&C GREEN NO. 3

DRUG FACTS

Active ingredients

Eucalyptol 0.092%, Menthol 0.042%, Methyl Salicylate 0.060%, Thymol 0.064%

Purpose

Antiplaque/Antigingivitis

Uses

to help reduce and prevent

- plaque
- gingivitis

Warnings

Do not use in children under 12 years of age.

Keep out of reach of children.

If more than used for rinsing is accidentally swallowed, get medical help or contact a Poison Control Center immediately.

Directions

- Rinse full strength for 30 seconds with 20 mL (2/3 fluid ounce or 4 teaspoonfuls) morning and night.
- Do not swallow.

Other information

- Store at room temperature.
- Cold weather may cloud this product. Its antiseptic properties are not affected.

Inactive ingredients

Water (Aqua), Alcohol (21.6%), Sorbitol, Flavor, Poloxamer 407, Benzoic Acid, Sodium Saccharin, Sodium Benzoate, Green 3 (CI 42053).

Questions or comments?

1-866-695-3030